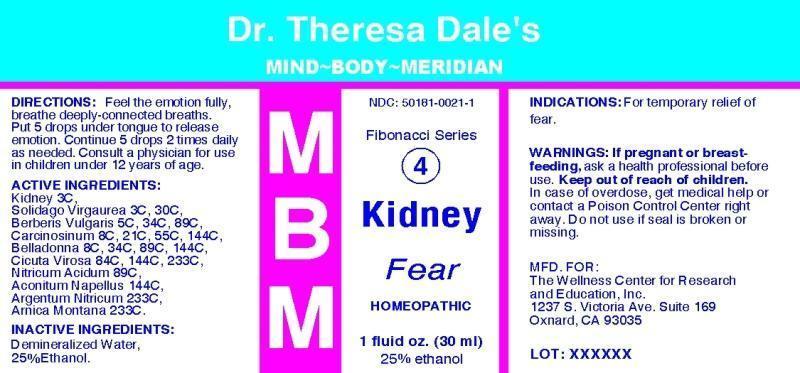 DRUG LABEL: MBM 4 Kidney
NDC: 50181-0021 | Form: LIQUID
Manufacturer: The Wellness Center
Category: homeopathic | Type: HUMAN OTC DRUG LABEL
Date: 20250529

ACTIVE INGREDIENTS: PORK KIDNEY 3 [hp_C]/1 mL; SOLIDAGO VIRGAUREA FLOWERING TOP 3 [hp_C]/1 mL; BERBERIS VULGARIS ROOT BARK 5 [hp_C]/1 mL; HUMAN BREAST TUMOR CELL 8 [hp_C]/1 mL; ATROPA BELLADONNA WHOLE 8 [hp_C]/1 mL; CICUTA VIROSA ROOT 84 [hp_C]/1 mL; NITRIC ACID 89 [hp_C]/1 mL; ACONITUM NAPELLUS 144 [hp_C]/1 mL; SILVER NITRATE 233 [hp_C]/1 mL; ARNICA MONTANA 233 [hp_C]/1 mL
INACTIVE INGREDIENTS: WATER; ALCOHOL

Drug Facts

ACTIVE INGREDIENTS:

Kidney (suis) 3C, Solidago virgaurea 3C, 30C, Berberis vulgaris 5C, 34C, 89C, Carcinosinum 8C, 21C, 55C, 144C, Belladonna 8C, 34C, 89C, 144C, Cicuta virosa 84C, 144C, 233C, Nitricum acidum 89C, Aconitum napellus 144C, Argentum nitricum 233C, Arnica montana 233C.

INDICATIONS:

For temporary relief of fear.

WARNINGS:

If pregnant or breast-feeding, ask a health professional before use.

Keep out of reacfh of children. In case of overdose, get medical help or contafct a Poison Control Center right away.

Do not use if seal is broken or missing.

DIRECTIONS:

Feel the emotion fully, breathe deeply-connected breaths. Put 5 drops under tongue to release emotion. Continue 5 drops 2 times daily as needed. Consult a physician for use in children under 12 years of age.

INACTIVE INGREDIENTS:

Demineralized water, 25% Ethanol.

KEEP OUT OF REACH OF CHILDREN.

In case of overdose, get medical help or contact a Poison Control Center right away.

INDICATIONS:

For temporary relief of fear.

QUESTIONS:

MFD. FOR:

The Wellness Center for Research and Education, Inc.

1237 S Victoria Ave. Suite 169

Oxnard, CA 93035

PACKAGE LABEL DISPLAY

Dr. Theresa Dale's

MIND-BODY-MERIDIAN

MBM

NDC: 50181-0021-1

Fibonaci Series

4

Kidney

Fear

HOMEOPATHIC

1 fluid oz. (30 ml)